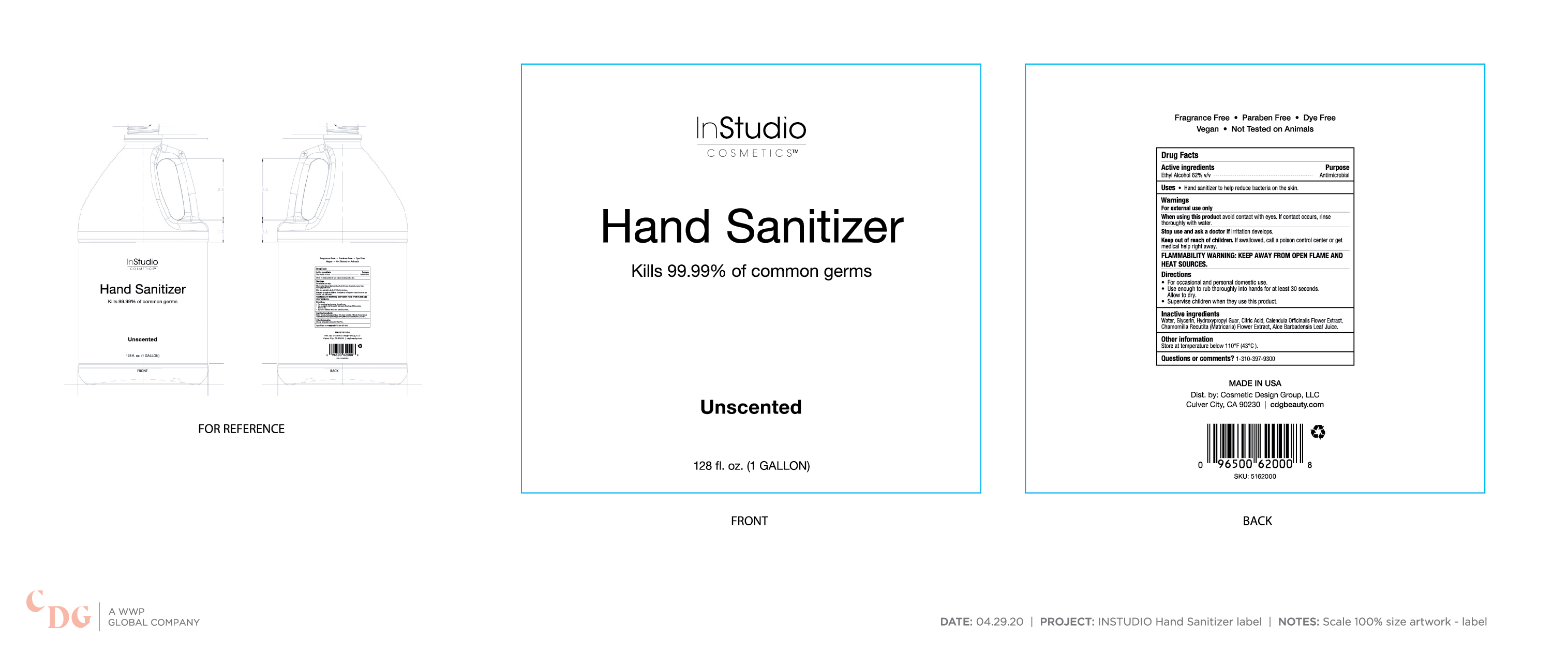 DRUG LABEL: 62% Unscented
NDC: 76150-246 | Form: GEL
Manufacturer: Bell International Laboratories, Inc.
Category: otc | Type: HUMAN OTC DRUG LABEL
Date: 20200511

ACTIVE INGREDIENTS: ALCOHOL 62 mL/100 mL
INACTIVE INGREDIENTS: WATER; ALOE VERA LEAF; CITRIC ACID MONOHYDRATE; CALENDULA OFFICINALIS FLOWER; CHAMOMILE; GLYCERIN; GUARAPROLOSE (1300 MPA.S AT 1%)

Cosmetic Design Group 62% Hand Sanitizer Gel Unscented

Active ingredients

Ethyl Alcohol 62% v/v

Purpose

Antimicrobial

Uses

Hand Sanitizer to help reduce bacteria on the skin

Warnings

For external use only

When using this product avoid contact with eyes. If contact occurs, rinse thoroughly with water.

Stop use and ask a doctor if irritation develops.

Flammability Warning: keep away from open flame and heat sources.

Keep out of reach of children. If swallowed, call a poison control center or get medical help right away.

Directions

For occasional and personal domestic use.

Use enough to rub thoroughly into hands for at least 30 seconds. Allow to dry

Supervise children when they use this product.

Inactive Ingredients

Water, Glycerin, Hydroxypropyl Guar, Citric Acid, Calendula Officinalis Flower Extract, Chamomilla Recutita (Matricaria) Flower Extract, Aloe Barbadensis Leaf Juice.

Other Information

Store at temperature below 110 F (43 C)